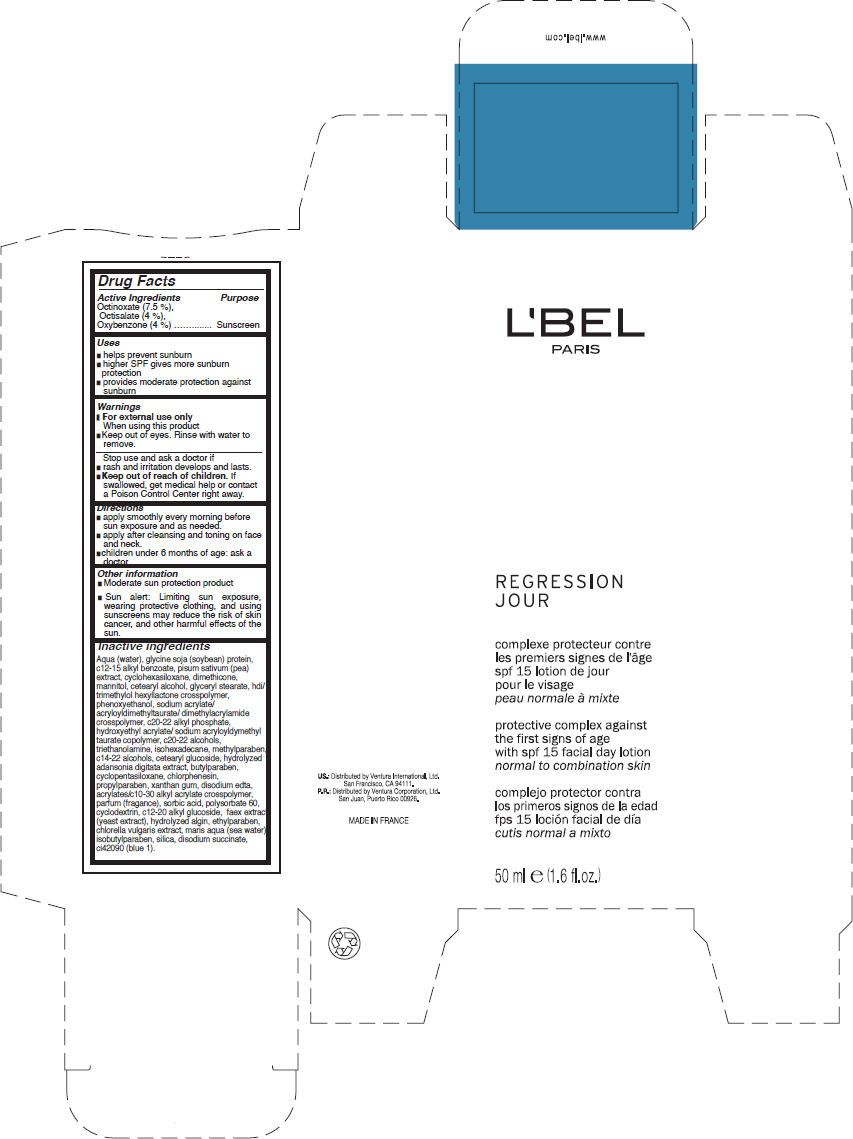 DRUG LABEL: LBel Paris 
NDC: 14783-055 | Form: CREAM
Manufacturer: Ventura International LTD
Category: otc | Type: HUMAN OTC DRUG LABEL
Date: 20100810

ACTIVE INGREDIENTS: Octinoxate 3.75 g/50 g; Octisalate 2 g/50 g; Oxybenzone 2 g/50 g
INACTIVE INGREDIENTS: water; soybean; c12-15 alkyl benzoate; snow pea; cyclomethicone 6; dimethicone; mannitol; cetostearyl alcohol; glyceryl monostearate; phenoxyethanol; trolamine; isohexadecane; methylparaben; butylparaben; cyclomethicone 5; chlorphenesin; propylparaben; xanthan gum; edetate disodium; sorbic acid; polysorbate 60; yeast; ethylparaben; isobutylparaben; silicon dioxide; sodium succinate anhydrous; FD&C blue no. 1

L'BEL
PARIS
REGRESSION
JOUR

Drug Facts

Active Ingredients

Octinoxate (7.5 %), Octisalate (4 %), Oxybenzone (4 %)

Purpose

Sunscreen

Uses

- helps prevent sunburn
- higher SPF gives more sunburn protection
- provides moderate protection against sunburn

Warnings

- For external use only.

When using this product

- keep out of eyes. Rinse with water to remove.

Stop use and ask a doctor if

- rash and irritation develops and lasts.

- Keep out of reach of children. If swallowed, get medical help or contact a Poison Control Center right away.

Directions

- apply smoothly every morning before sun exposure and as needed.
- apply after cleansing and toning on face and neck.
- children under 6 months of age: ask a doctor.

Other information

- Moderate sun protection product.
- Sun alert: Limiting sun exposure, wearing protective clothing, and using sunscreens may reduce the risk of skin cancer, and other harmful effects of the sun.

Inactive ingredients

Aqua (water), glycine soja (soybean) protein, c12-15 alkyl benzoate, pisum sativum (pea) extract, cyclohexasiloxane, dimethicone, mannitol, cetearyl alcohol, glyceryl stearate, hdi/ trimethylol hexyllactone crosspolymer, phenoxyethanol, sodium acrylate/ acryloyldimethyltaurate/ dimethylacrylamide crosspolymer, c20-22 alkyl phosphate, hydroxyethyl acrylate/ sodium acryloyldymethyl taurate copolymer, c20-22 alcohols, triethanolamine, isohexadecane, methylparaben, c14-22 alcohols, cetearyl glucoside, hydrolyzed adansonia digitata extract, butylparaben, cyclopentasiloxane, chlorphenesin, propylparaben, xanthan gum, disodium edta, acrylates/c10-30 alkyl acrylate crosspolymer, parfum (fragance), sorbic acid, polysorbate 60, cyclodextrin, c12-20 alkyl glucoside, faex extract (yeast extract), hydrolyzed algin, ethylparaben, chlorella vulgaris extract, maris aqua (sea water), isobutylparaben, silica, disodium succinate, ci42090 (blue 1).

US: Distributed by Ventura International, Ltd. San Francisco, CA 94111

PRINCIPAL DISPLAY PANEL - 50 ml Carton

L'BEL
PARIS

REGRESSION
JOUR

protective complex against
the first signs of age
with spf 15 facial day lotion
normal to combination skin

50 ml e (1.6 fl.oz.)